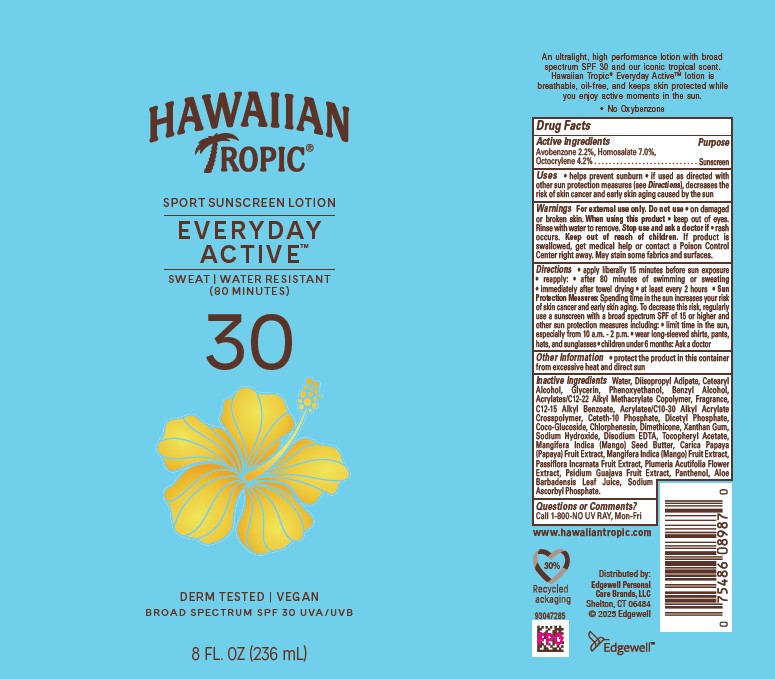 DRUG LABEL: Hawaiian Tropic Everyday Active SPF30
NDC: 63354-054 | Form: LOTION
Manufacturer: Edgewell Personal Care Brands LLC
Category: otc | Type: HUMAN OTC DRUG LABEL
Date: 20251105

ACTIVE INGREDIENTS: AVOBENZONE 2.2 g/100 g; HOMOSALATE 7 g/100 g; OCTOCRYLENE 4.2 g/100 g
INACTIVE INGREDIENTS: PLUMERIA RUBRA FLOWER; GUAVA; MANGIFERA INDICA SEED BUTTER; DIMETHICONE; PASSIFLORA INCARNATA FRUIT; COCO GLUCOSIDE; PAPAYA; MANGO; PANTHENOL; ALOE VERA LEAF; DIISOPROPYL ADIPATE; CETOSTEARYL ALCOHOL; PHENOXYETHANOL; BENZYL ALCOHOL; DIHEXADECYL PHOSPHATE; CHLORPHENESIN; EDETATE DISODIUM ANHYDROUS; .ALPHA.-TOCOPHEROL ACETATE; SODIUM HYDROXIDE; SODIUM ASCORBYL PHOSPHATE; WATER; GLYCERIN; ALKYL (C12-15) BENZOATE; CETETH-10 PHOSPHATE; XANTHAN GUM

Active Ingredients

Avobenzone 2.2%, Homosalate 7.0%, Octocrylene 4.2%

Purpose

Sunscreen

Uses

• helps prevent sunburn • if used as directed with other sun protection measures (see Directions), decreases the risk of skin cancer and early skin aging caused by the sun

Warnings

For external use only

May stain some fabrics.

Do not use

on damaged or broken skin

When using this product

do not get into eyes. If contact occurs, rinse thoroughly with water

Stop use and ask a doctor

if irritation or rash develops

Keep out of reach of children

If swallowed, get medical help or contact a Poison Control Center right away.

Directions

• apply liberally 15 minutes before sun exposure • reapply: • after 80 minutes of swimming or sweating • immediately after towel drying • at least every 2 hours • Sun Protection Measures: Spending time in the sun increases your risk of skin cancer and early skin aging. To decrease this risk, regularly use a sunscreen with a broad spectrum SPF of 15 or higher and other sun protection measures including: • limit time in the sun, especially from 10 a.m. - 2 p.m. • wear long-sleeved shirts, pants, hats, and sunglasses • children under 6 months: Ask a doctor

Inactive Ingredients

Water, Diisopropyl Adipate, Cetearyl Alcohol, Glycerin, Phenoxyethanol, Benzyl Alcohol, Acrylates/C12-22 Alkyl Methacrylate Copolymer, Fragrance, C12-15 Alkyl Benzoate, Acrylates/C10-30 Alkyl Acrylate Crosspolymer, Ceteth-10 Phosphate, Dicetyl Phosphate, Coco-Glucoside, Chlorphenesin, Dimethicone, Xanthan Gum, Sodium Hydroxide, Disodium EDTA, Tocopheryl Acetate, Mangifera Indica (Mango) Seed Butter, Carica Papaya (Papaya) Fruit Extract, Mangifera Indica (Mango) Fruit Extract, Passiflora Incarnata Fruit Extract, Plumeria Acutifolia Flower Extract, Psidium Guajava Fruit Extract, Panthenol, Aloe Barbadensis Leaf Juice, Sodium Ascorbyl Phosphate.

Other Information

• protect this product from excessive heat and direct sun

Questions or Comments?

Call 1-800-NO UV RAY, Mon-Fri

PRINCIPAL DISPLAY PANEL

HAWAIIAN
TROPIC®
SPORT SUNSCREEN LOTION
EVERYDAY
ACTIVE
SWEAT | WATER RESISTANT
(80 MINUTES)
30
DERM TESTED | VEGAN
BROAD SPECTRUM SPF 30 UVA/UVB
8 FL. OZ (236 mL)